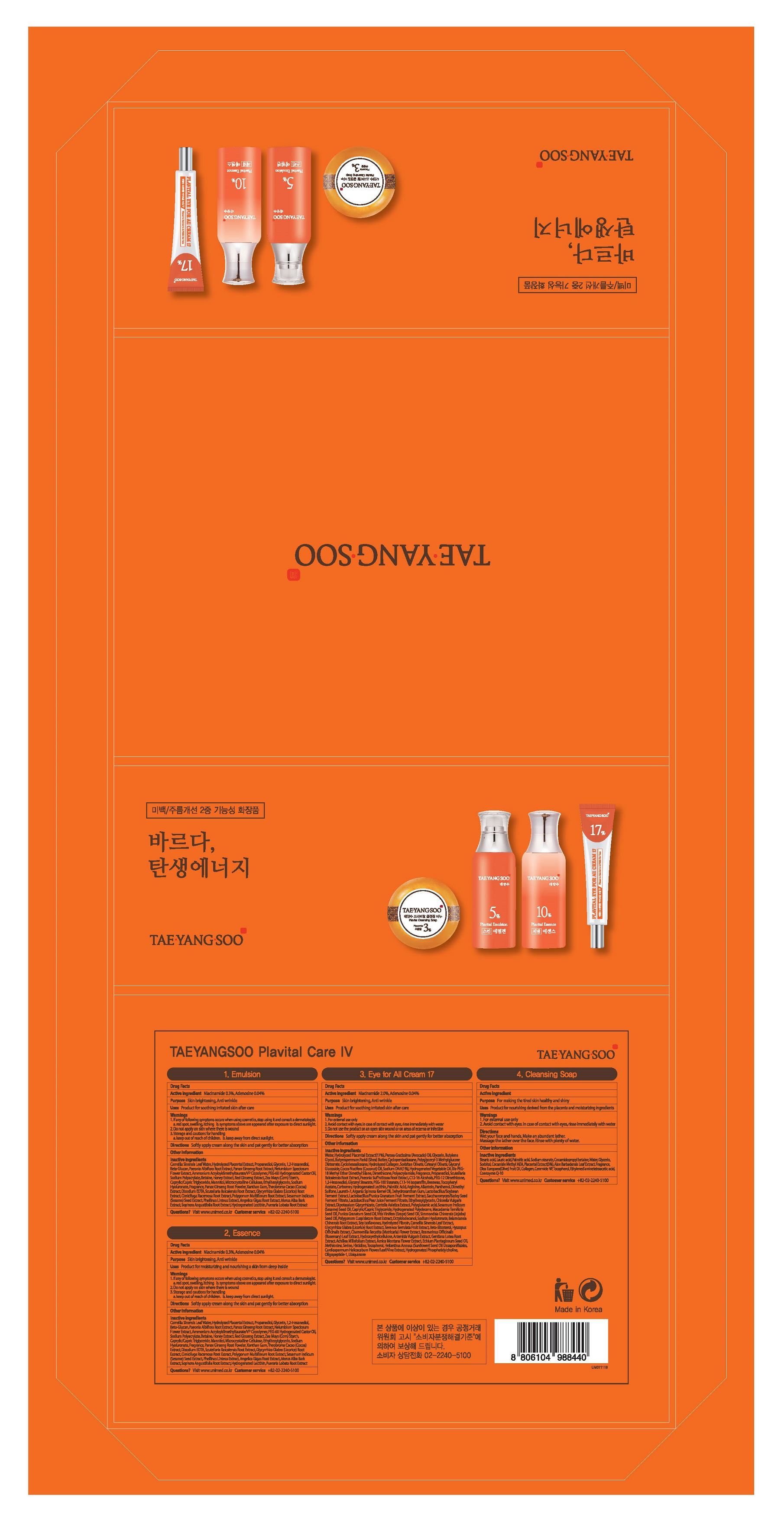 DRUG LABEL: TAEYANGSOO Plavital Essence
NDC: 73669-002 | Form: EMULSION
Manufacturer: Unimed Pharmaceuticals, Inc.
Category: otc | Type: HUMAN OTC DRUG LABEL
Date: 20200927

ACTIVE INGREDIENTS: NIACINAMIDE 0.3 g/100 mL; ADENOSINE 0.04 g/100 mL
INACTIVE INGREDIENTS: WATER

Drug Facts

ACTIVE INGREDIENT

adenosine, niacinamide

INACTIVE INGREDIENT

Camellia Sinensis Leaf Water
1,2-Hexanediol
Water
Hydrolyzed Placental Extract
1,2-Hexanediol
Propanediol
Glycerin
1,2-Hexanediol
Beta-Glucan
Water
1,2-Hexanediol
Paeonia Albiflora Root Extract
Water
1,2-Hexanediol
Panax Ginseng Root Extract
Water
1,2-Hexanediol
Nelumbium Speciosum Flower Extract
Ammonium Acryloyldimethyltaurate/VP Copolymer
PEG-60 Hydrogenated Castor Oil
Sodium Polyacrylate
Betaine
Water
1,2-Hexanediol
Honey Extract
Water
1,2-Hexanediol
Panax Ginseng Root Extract
Zea Mays (Corn) Starch
Mannitol
Microcrystalline Cellulose
Panax Ginseng Root Powder
Hydrogenated Lecithin
Scutellaria Baicalensis Root Extract
Pueraria Lobata Root Extract
Caprylic/Capric Triglyceride
Ethylhexylglycerin
Sodium Hyaluronate
Fragrance
Xanthan Gum
Theobroma Cacao (Cocoa) Extract
Disodium EDTA
Water
Scutellaria Baicalensis Root Extract
Glycyrrhiza Glabra (Licorice) Root Extract
Cimicifuga Racemosa Root Extract
Polygonum Multiflorum Root Extract
Sesamum Indicum (Sesame) Seed Extract
Phellinus Linteus Extract
Angelica Gigas Root Extract
Morus Alba Bark Extract
Paeonia Albiflora Root Extract
Sophora Angustifolia Root Extract
1,2-Hexanediol

PURPOSE

anti-wrinkle, whitening

keep out of reach of the children

INDICATIONS AND USAGE

apply proper amount to the skin

WARNINGS

For external use only
When using this product

■ if the following symptoms occurs after use, stop use and consult with a skin specialist

red specks, swelling, itching

■ don’t use on the part where there is injury, eczema, or dermatitis

Keep out of reach of children

■ if swallowed, get medical help or contact a person control center immediately

DOSAGE AND ADMINISTRATION

external use only